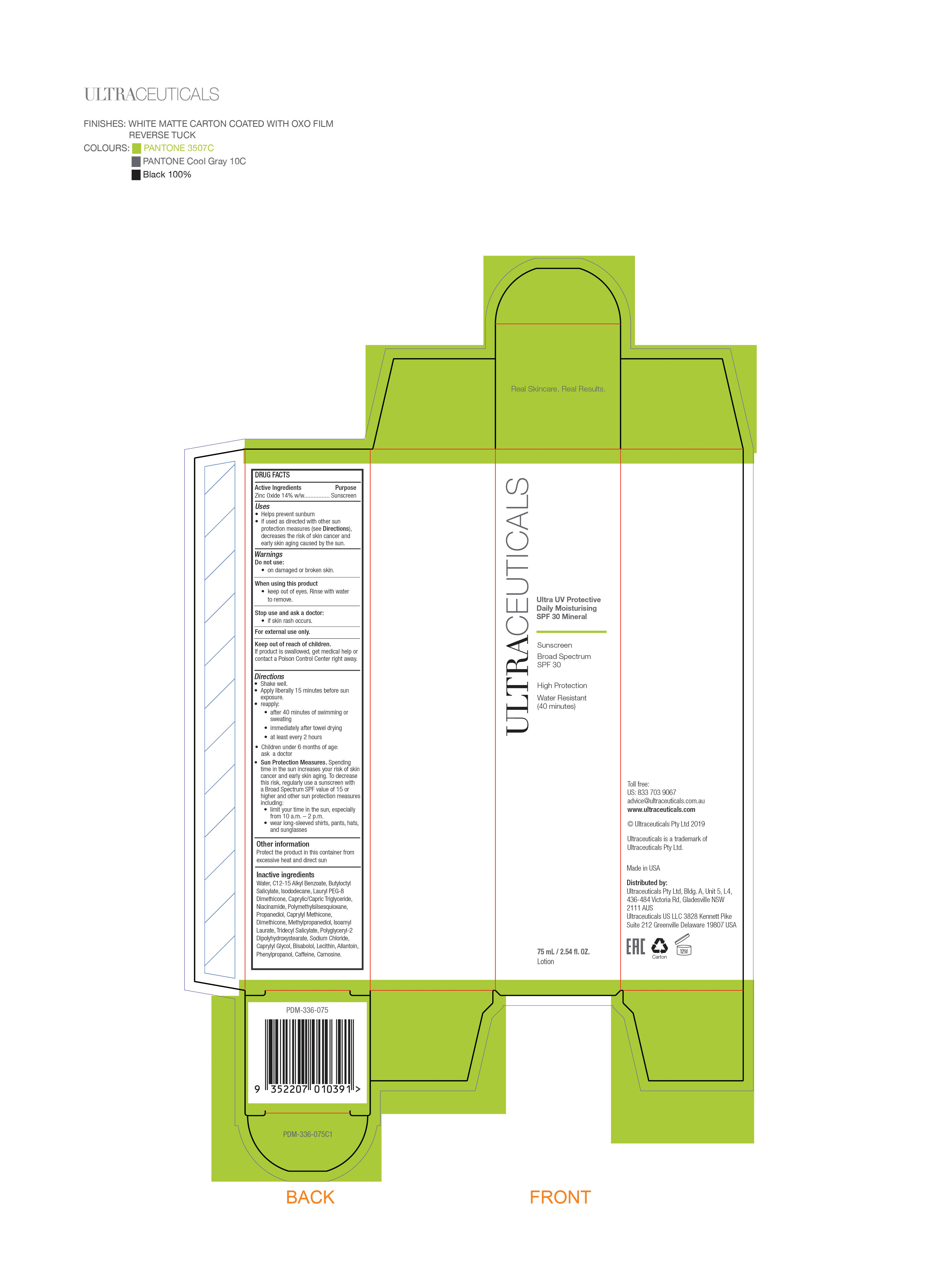 DRUG LABEL: Ultra UV Protective Daily Moisturising SPF 30 Mineral Sunscreen
NDC: 10028-030 | Form: CREAM
Manufacturer: Ultraceuticals Pty Ltd
Category: otc | Type: HUMAN OTC DRUG LABEL
Date: 20250605

ACTIVE INGREDIENTS: ZINC OXIDE 14 g/100 mL
INACTIVE INGREDIENTS: SODIUM CHLORIDE; SOYBEAN LECITHIN; CARNOSINE; ALKYL (C12-15) BENZOATE; ISOAMYL LAURATE; BISABOLOL; POLYGLYCERYL-2 DIPOLYHYDROXYSTEARATE; PHENYLPROPANOL; WATER; BUTYLOCTYL SALICYLATE; PROPANEDIOL; ISODODECANE; MEDIUM-CHAIN TRIGLYCERIDES; NIACINAMIDE; POLYMETHYLSILSESQUIOXANE (11 MICRONS); CAPRYLYL METHICONE; DIMETHICONE; METHYLPROPANEDIOL; ALLANTOIN; CAFFEINE; CAPRYLYL GLYCOL; LAURYL PEG-8 DIMETHICONE (300 CPS); TRIDECYL SALICYLATE

Ultra UV Protective Daily Moisturising SPF 30 Mineral Lotion

Active Ingredients Purpose
Zinc Oxide 14% w/w................ Sunscreen

Uses
• Helps prevent sunburn
• if used as directed with other sun
protection measures (see Directions),
decreases the risk of skin cancer and
early skin aging caused by the sun.

Keep out of reach of children.
If product is swallowed, get medical help or contact a Poison Control Center right away.

Stop use and ask a doctor:
• if skin rash occurs.

Warnings

Do not use:

• on damaged or broken skin.

When using this product

• keep out of eyes. Rinse with water

to remove.

For external use only.

Directions
• Shake well.
• Apply liberally 15 minutes before sun
exposure.
reapply:
• Sun Protection Measures. Spending
time in the sun increases your risk of skin
cancer and early skin aging. To decrease
this risk, regularly use a sunscreen with
a Broad Spectrum SPF value of 15 or
higher and other sun protection measures
including:
• limit your time in the sun, especially
from 10 a.m. – 2 p.m.
• wear long-sleeved shirts, pants, hats,
and sunglasses
• after 40 minutes of swimming or
sweating
• immediately after towel drying
• at least every 2 hours
• Children under 6 months of age:
ask a doctor

Inactive ingredients
Water, C12-15 Alkyl Benzoate, Butyloctyl Salicylate, Isododecane, Lauryl PEG-8 Dimethicone, Caprylic/Capric Triglyceride,
Niacinamide, Polymethylsilsesquioxane, Propanediol, Caprylyl Methicone, Dimethicone, Methylpropanediol, Isoamyl Laurate, Tridecyl Salicylate, Polyglyceryl-2 Dipolyhydroxystearate, Sodium Chloride, Caprylyl Glycol, Bisabolol, Lecithin, Allantoin, Phenylpropanol, Caffeine, Carnosine.

PACKAGE LABEL

Ultraceuticals

Ultra UV Protective Daily Moisturisingg SPF 30 Mineral sunscreen Lotion

Broad Spectrum SPF 30

High Protection

Water Resistant

75 mL / 2.54 fl. Oz.

Lotion